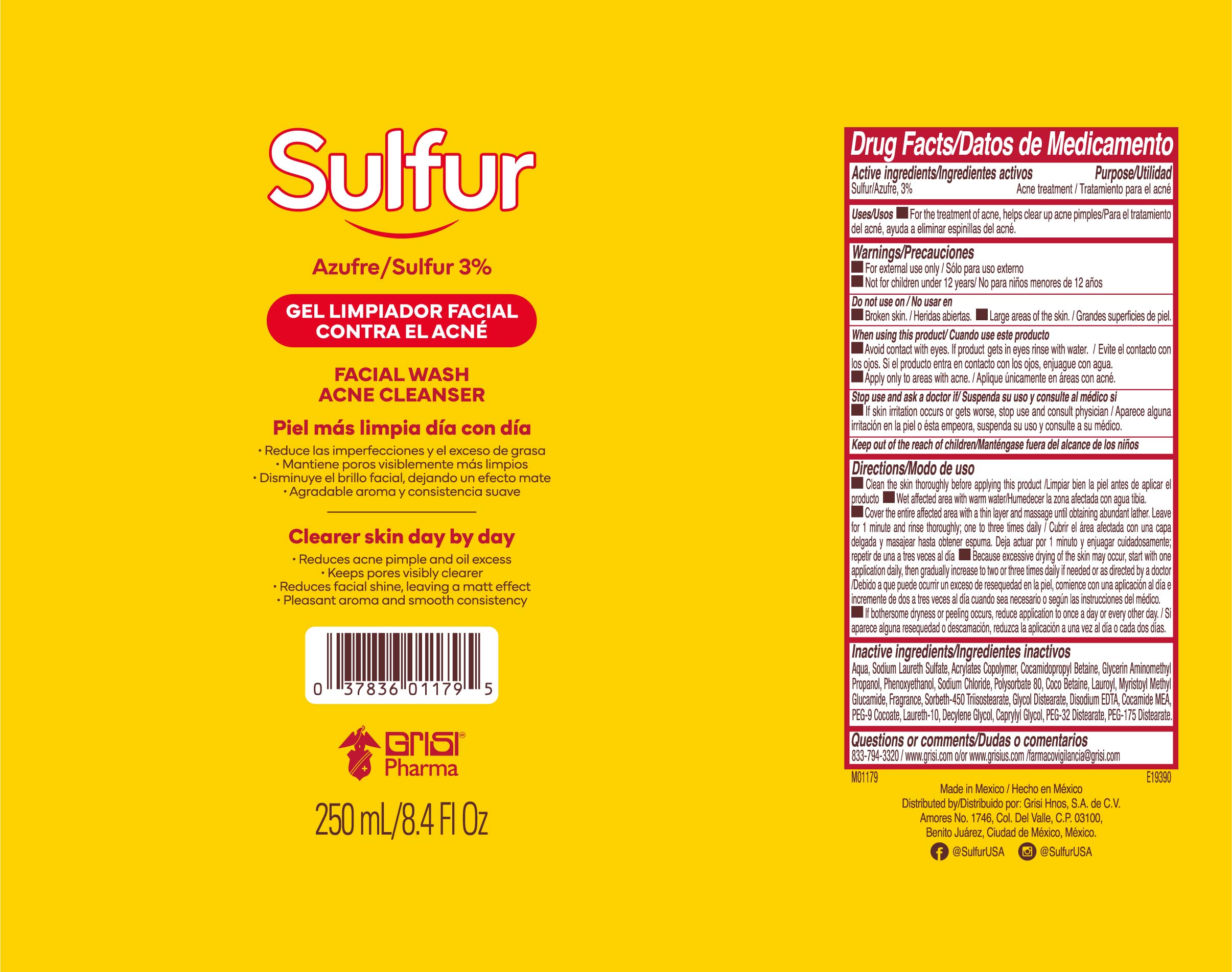 DRUG LABEL: Sulfur Facial Wash
NDC: 84663-001 | Form: LIQUID
Manufacturer: Industria Farmacéutica Andromaco, S.A. de C.V.
Category: otc | Type: HUMAN OTC DRUG LABEL
Date: 20250114

ACTIVE INGREDIENTS: SULFUR 3 g/100 mL
INACTIVE INGREDIENTS: PEG-32 DISTEARATE; PEG-175 DISTEARATE; EDETATE SODIUM; SODIUM CHLORIDE; WATER; AMINOMETHYLPROPANOL; PHENOXYETHANOL; CAPRYLYL GLYCOL; COCO MONOETHANOLAMIDE; COCAMIDOPROPYL BETAINE; COCO-BETAINE; DECYLENE GLYCOL; GLYCERIN; GLYCOL DISTEARATE; LAURETH-10; LAUROYL/MYRISTOYL METHYL GLUCAMIDE; POLYSORBATE 80; SODIUM LAURETH SULFATE

Sulfur Facial Wash

Active ingredients/Ingredientes activos

Sulfur/Azufre 3%

Purpose/Utilidad

Acne treatment/Tratamiento para el acné

Uses/Usos

■ For the treatment of acne, helps clear up acne pimples/Para el tratamiento del acne, ayuda e eliminar espinillas del acne

Warnings/Precauciones

■ For external use only/Solo par uso externo

■ Not for children under 12 years/No par ninos menores de 12 anos

Do not use/No user en

■ Broken skin/Heridas abiertas ■ Large areas of the skin/Grandes superficies de piel

When using this product/Cuando use este producto

■ Avoid contact with the eyes. If product gets in the eyes rinse with water/Evite el contacto con los ojos. Si el producto entra en contacto con los ojos, enjuague con agua.
■ Apply only to the areas with acne/Aplique únicamente en áreas con acné

St op use and ask a doctor if/Suspenda su uso y consulte al medico si

■ if skin irritation occurs or gets worse, stop use and consult a physician/Aparece alguna irritacion en la piel o esta empeora, suspenda su uso y consulte a su medico.

Keep out of the reach of children

Mantengase fuera del alcance de los ninos

Directions/Modo de uso

■ Clean the skin thoroughly before applying this product/Limpiar bien la piel antes de aplicar el producto.

■ Wet affected area with warm water/Humedecer la zona afectada con aqua tibia.

■ Cover the entire affected area with a thin layer and massage until obtaining abundant lather. Leave for 1 minute and rinse thoroughly; one to three times a day/Cubrir el area afectada con una capa delgada y masajear hasta obtener espuma. Deja actuar por 1 minuto y enjuagar cuidadosamente; repetir de una a tres veces al dia ■ Because excessive drying of the skin may occur, start with one application daily, then gradually increase to two or three times daily if needed or as directed by a doctor/Debido a que puede ocurrir un exceso de resequedad en la piel, comience con una aplicación al día e incremente de los a tres veces al dia cuando sea necesario o segun las indicaciones del médico

■ If bothersome dryness or peeling occurs, reduce application to once a day or every other day/Si aparece alguna resequedad o descamación, reduzca la aplicación a una vez al día o cada dos días

Inactive Ingredients/Ingredientes inactivos

Aqua, Sodium Laureth Sulfate, Acrylates Copolymer, Cocamidopropyl Betaine, Glycerin Aminomethyl Propanol, Phenoxyethanol, Sodium Chloride, Polysorbate 80, Coco Betaine, Lauroyl, Myristoyl Methyl Glucamide, Fragrance, Sorbeth-450 Triisostearate, Glycol Distearate, Disodium EDTA, Cocamide MEA, PEG-9 Cocoate, Laureth-10, Decylene Glycol, Caprylyl Glycol, PEG-32 Distearate, PEG-175 Distearate.

Questions or comments/Dudas o comentarios

833-794-3320/www.grisi.com o/or www.grisius.com/farmacoviglancia@grisi.com